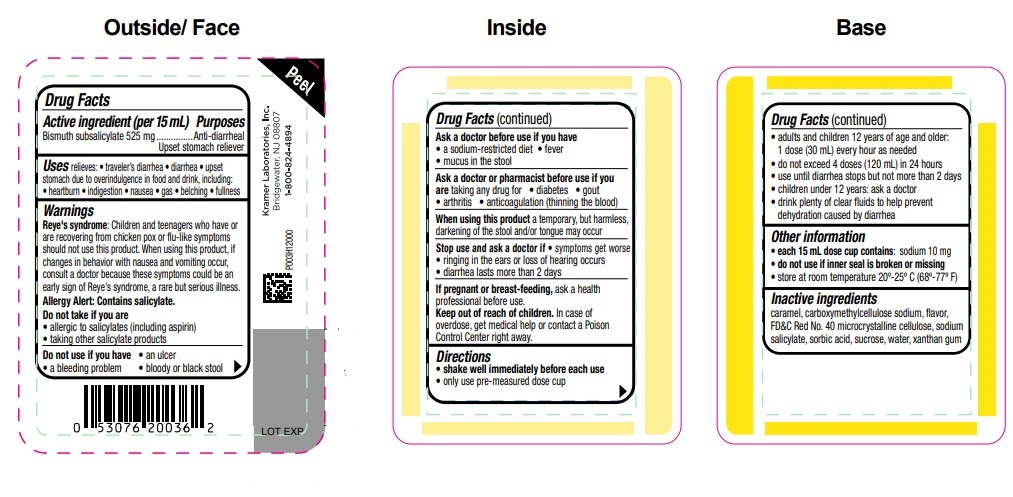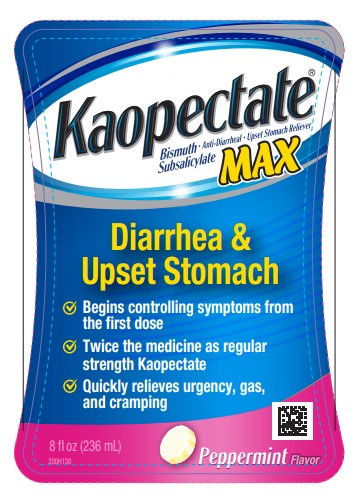 DRUG LABEL: Kaopectate Max Peppermint Flavor Anti Diarrheal
NDC: 55505-200 | Form: LIQUID
Manufacturer: Kramer Laboratories
Category: otc | Type: HUMAN OTC DRUG LABEL
Date: 20251219

ACTIVE INGREDIENTS: BISMUTH SUBSALICYLATE 525 mg/15 mL
INACTIVE INGREDIENTS: CARAMEL; Carboxymethylcellulose Sodium, Unspecified Form; Fd&C Red No. 40; Microcrystalline Cellulose; SODIUM SALICYLATE; SORBIC ACID; SUCROSE; WATER; XANTHAN GUM

Drug Facts

ACTIVE INGREDIENT

Active ingredient (per 15 mL) | Purposes
Bismuth subsalicylate 525 mg | Anti-diarrheal Upset stomach reliever

INDICATIONS AND USAGE

Uses relieves

- traveler’s diarrhea
- diarrhea
- upset stomach due to overindulgence in food and drink, including:
  - heartburn
  - indigestion
  - nausea
  - gas
  - belching
  - fullness

Reye's syndrome: Children and teenagers who have or are recovering from chicken pox or flu-like symptoms should not use this product. When using this product, if changes in behavior with nausea and vomiting occur, consult a doctor because these symptoms could be an early sign of Reye's syndrome, a rare but serious illness.

Do not take if you are

- allergic to salicylates (including aspirin)
- taking other salicylate products

Do not use if you have

- an ulcer
- a bleeding problem
- bloody or black stool

Ask a doctor before use if you have

- a sodium-restricted diet
- fever
- mucus in the stool

Ask a doctor or pharmacist before use if you are taking any drug for

- diabetes
- gout
- arthritis
- anticoagulation (thinning the blood)

When using this product a temporary, but harmless, darkening of the stool and/or tongue may occur

Stop use and ask a doctor if

- symptoms get worse
- ringing in the ears or loss of hearing occurs
- diarrhea lasts more than 2 days

PREGNANCY OR BREAST FEEDING

If pregnant or breast-feeding, ask a health professional before use.

Keep out of reach of children. In case of overdose, get medical help or contact a Poison Control Center right away.

Directions

- shake well immediately before each use
- only use pre-measured dose cup
- adults and children 12 years of age and older:
  - 1 dose (30 mL) every hour as needed
  - do not exceed 4 doses (120 mL) in 24 hours
  - use until diarrhea stops but not more than 2 days
  - children under 12 years: ask a doctor
  - drink plenty of clear fluids to help prevent dehydration caused by diarrhea

Other Information

- each 15 mL dose cup contains: sodium 10 mg
- do not use if inner seal is broken or missing
- store at room temperature 20º-25º C (68º-77º F)

Inactive Ingredients

caramel, carboxymethylcellulose sodium, flavor, FD&C Red No. 40 microcrystalline cellulose, sodium salicylate, sorbic acid, sucrose, water, xanthan gum

Principal Display Panel

Kaopectate®
Bismuth Subsalicylate
• Anti-Diarrheal • Upset Stomach Reliever
MAX
Diarrhea &
Upset Stomach
✓ Begins controlling symptoms from the first dose
✓ Twice the medicine as regular strength Kaopectate
✓ Quickly relieves urgency, gas, and cramping
8 fl oz (236 mL)
Peppermint Flavor
200H130

Peel
Kramer Laboratories, Inc.
Bridgewater, NJ 08807
1-800-824-4894
LOT EXP
P003H12000